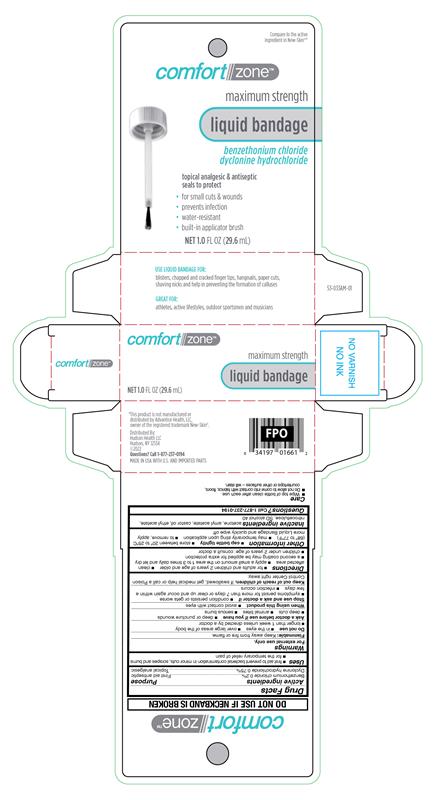 DRUG LABEL: Benzethonium chloride Plus Dyclonine hydrochloride
NDC: 72446-100 | Form: LIQUID
Manufacturer: Hudson Health LLC
Category: otc | Type: HUMAN OTC DRUG LABEL
Date: 20251020

ACTIVE INGREDIENTS: BENZETHONIUM CHLORIDE 2 mg/1 mL; DYCLONINE HYDROCHLORIDE 7.5 mg/1 mL
INACTIVE INGREDIENTS: AMYL ACETATE; CASTOR OIL; ETHYL ACETATE; PYROXYLIN; ALCOHOL; ACETONE

Comfortzone Liquid Bandage

Active ingredients

Benzethonium chloride 0.2%

Dyclonine hydrochloride 0.75%

Purpose

First aid antiseptic

Topical analgesic

Uses

- first aid to prevent bacteria contamination in minor cuts, scrapes and burns
- for the temporary relief of pain

Warnings

For external use only.

Flammable:

Keep away from fire or flame.

Do not use

- in the eyes
- over large areas of the body
- longer than 1 week unless directed by a doctor

Ask a doctor before use if you have

- deep or puncture wounds
- deep cuts
- animal bites
- serious burns

When using this product

avoid contact with eyes

Stop use and ask a doctor if

- condition persists or gets worse
- symptoms persist for more than 7 days or clear up and occur again within a few days
- infection occurs

Keep out of reach of children.

If swallowed, get medical help or call a Poison Control Center right away.

Directions

- for adults and children 2 years of age and older
- clean affected area
- apply a small amount on the area 1 to 3 times daily and let dry
- a second coating may be applied for extra protection
- children under 2 years of age: consult a doctor

Other information

- cap bottle tightly
- store between 20C to 25C (68 TO 77F)
- may temporarily sting upon application
- to remove, apply more Liquid Bandage and quickly wipe off

Inactive ingredients

acetone, amyl acetate, castor oil, ethyl acetate, nitrocellulose, SD slcohol 40

Questions

1-877-237-0194

RECENT MAJOR CHANGES

.

Principal Display Panel

comfortzone

maximum strength

liquid bandage

benzethonium chloride

dyclonine hydrochloride

topical analgesic & antiseptic

seals to protect

- for small cut & wounds
- prevents infection
- water-resistant
- built-in applicator brush

NET 1.0 FL OZ (29.6 mL)